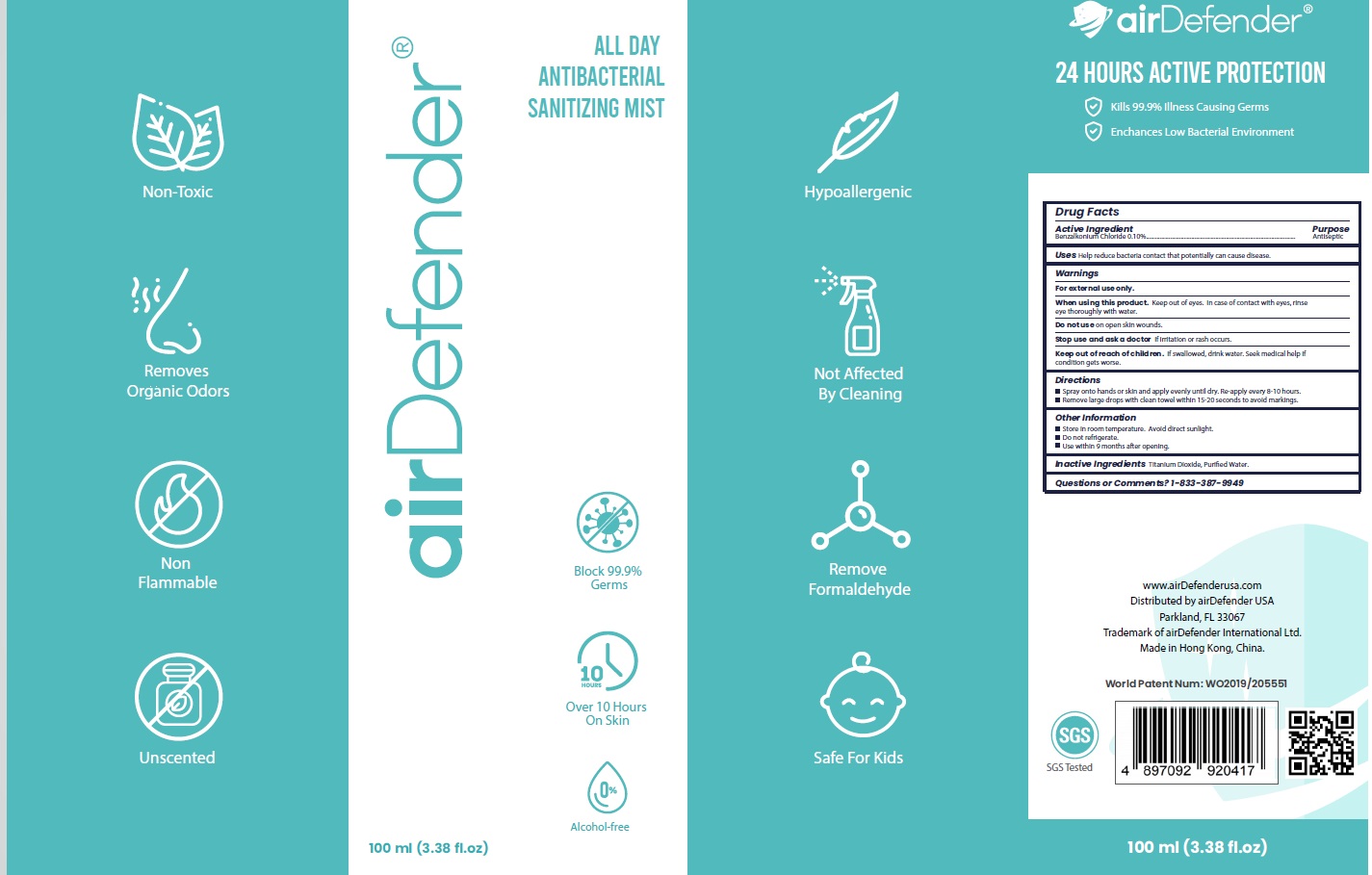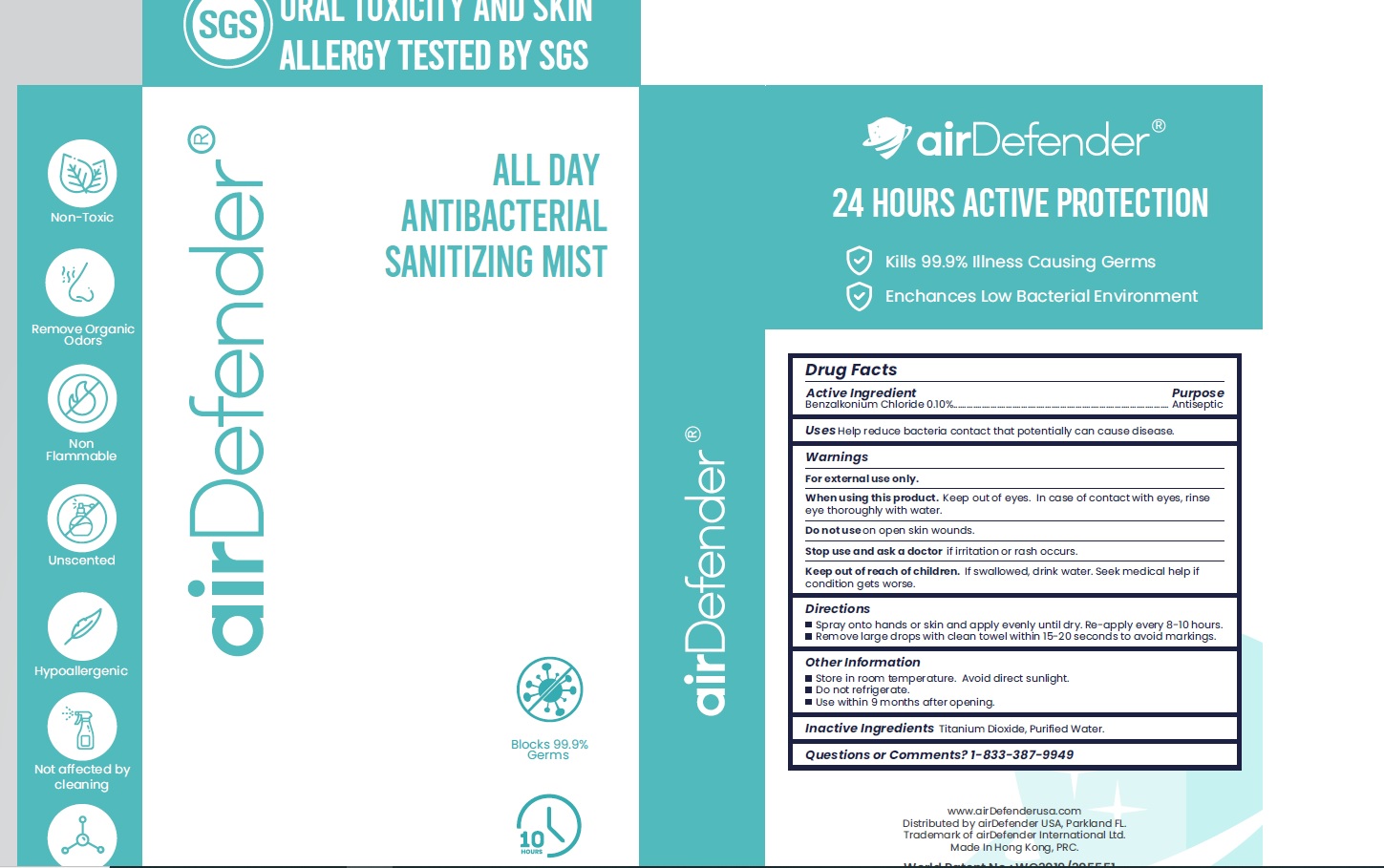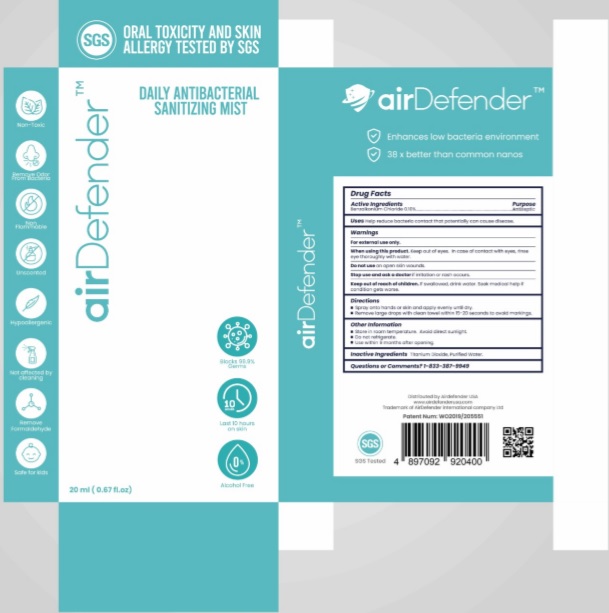 DRUG LABEL: airDefender Daily Antibacterial Sanitizing Mist
NDC: 78976-001 | Form: SPRAY
Manufacturer: Airdefender International Company Limited
Category: otc | Type: HUMAN OTC DRUG LABEL
Date: 20221130

ACTIVE INGREDIENTS: BENZALKONIUM CHLORIDE 1 mg/1 mL
INACTIVE INGREDIENTS: TITANIUM DIOXIDE; WATER

airDefender Daily Antibacterial Sanitizing Mist:
20 mL - 78976-001-20
100 mL - 78976-001-10

Active Ingredient(s)

Benzalkonium Chloride 0.10%

Purpose

Antiseptic

Use

Help reduce bacteria contact that potentially can cause disease.

Warnings

For external use only.

Do not use

- on open skin wounds

WHEN USING

Keep out of eyes. In case of contact with eyes, rinse eye thoroughly with water.

Stop use and ask a doctor if irritation or rash occurs.

KEEP OUT OF REACH OF CHILDREN

If swallowed, drink water. Seek medical help if condition gets worse.

Directions

- Spray onto hands or skin and apply evenly until dry.
- Remove large drops with clean towel within 15-20 seconds to avoid markings

Other information

- Store in room temperature. Avoid direct sunlight.
- Do not refrigerate.
- Use within 9 months after opening

Inactive ingredients

Titanium Dioxide, Purified Water

Questions or Comments?

1-833-387-9949

Package Label - Principal Display Panel

DISTRIBUTED BY: Airdefender USA

airDefender Daily Antibacterial Sanitizing Mist (20 mL) NDC: 78976-001-20

airDefender Daily Antibacterial Sanitizing Mist (100 mL) NDC: 78976-001-10

airDefender Daily Antibacterial Sanitizing Mist - OUTER CONTAINER